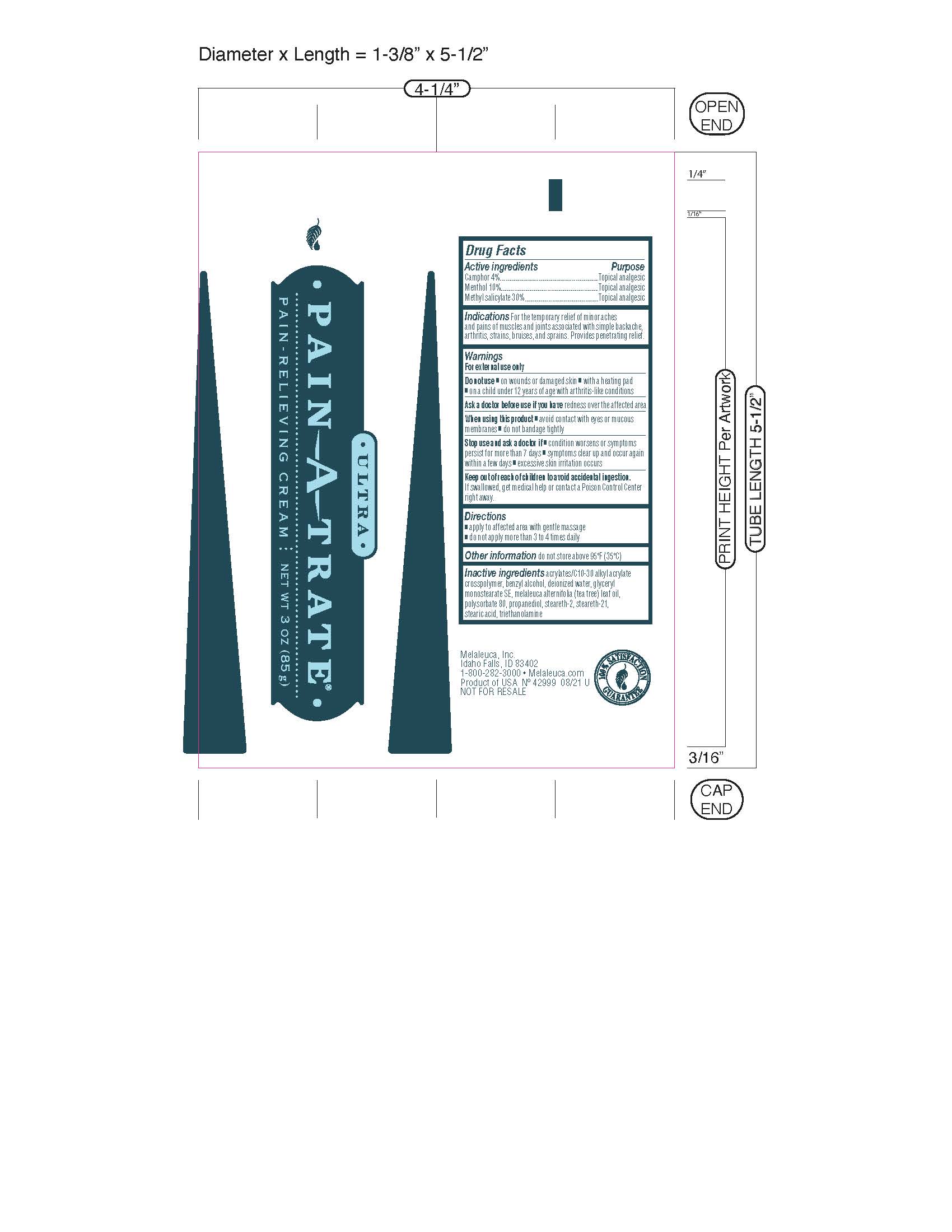 DRUG LABEL: Ultra Pain-A-Trate
NDC: 54473-334 | Form: CREAM
Manufacturer: Melaleuca, Inc.
Category: otc | Type: HUMAN OTC DRUG LABEL
Date: 20251231

ACTIVE INGREDIENTS: CAMPHOR (SYNTHETIC) 3.4 g/85 g; MENTHOL 8.5 g/85 g; METHYL SALICYLATE 25.5 g/85 g
INACTIVE INGREDIENTS: TROLAMINE; PROPANEDIOL; STEARETH-2; CARBOMER INTERPOLYMER TYPE A (ALLYL SUCROSE CROSSLINKED); WATER; STEARIC ACID; TEA TREE OIL; BENZYL ALCOHOL; GLYCERYL STEARATE SE; POLYSORBATE 80; STEARETH-21

Pain-A-Trate Ultra

Active ingredients
Camphor 4%
Menthol 10%
Methyl Salicylate 30%

Purpose
Topical analgesic

INDICATIONS AND USAGE

Indications For the temporary relief of minor aches and pains of muscles and joints associated with simple backache, arthritis, strains, bruises, and sprains. Provides penetrating relief.

Warnings
For external use only

Do not use

- on wounds or damaged skin
- with a heating pad
- on a child under 12 years of age with arthritis-like conditions

Ask a doctor before use if you have redness over the affected area.

When using this product

- avoid contact with eyes or mucus membranes
- do not bandage tightly

Stop use and ask a doctor if

- condition worsens or symptoms persist for more than 7 days
- symptoms clear up and occur again within a few days
- excessive skin irritation occurs

Keep out of reach of children to avoid accidental ingestion. If swallowed, get medical help or contact a Poison Control Center right away.

Directions

- apply to affected area with gentle massage
- do not apply more than 3 to 4 times daily

Other information do not store above 95°F (35°C)

INACTIVE INGREDIENT

Inactive ingredients acrylates/C10-30 alkyl acrylate crosspolymer, benzyl alcohol, deionized water, glyceryl monostearate SE, melaleuca alternifolia (tea tree) leaf oil, polysorbate 80, propanediol, steareth-2, steareth-21, stearic acid, triethanolamine